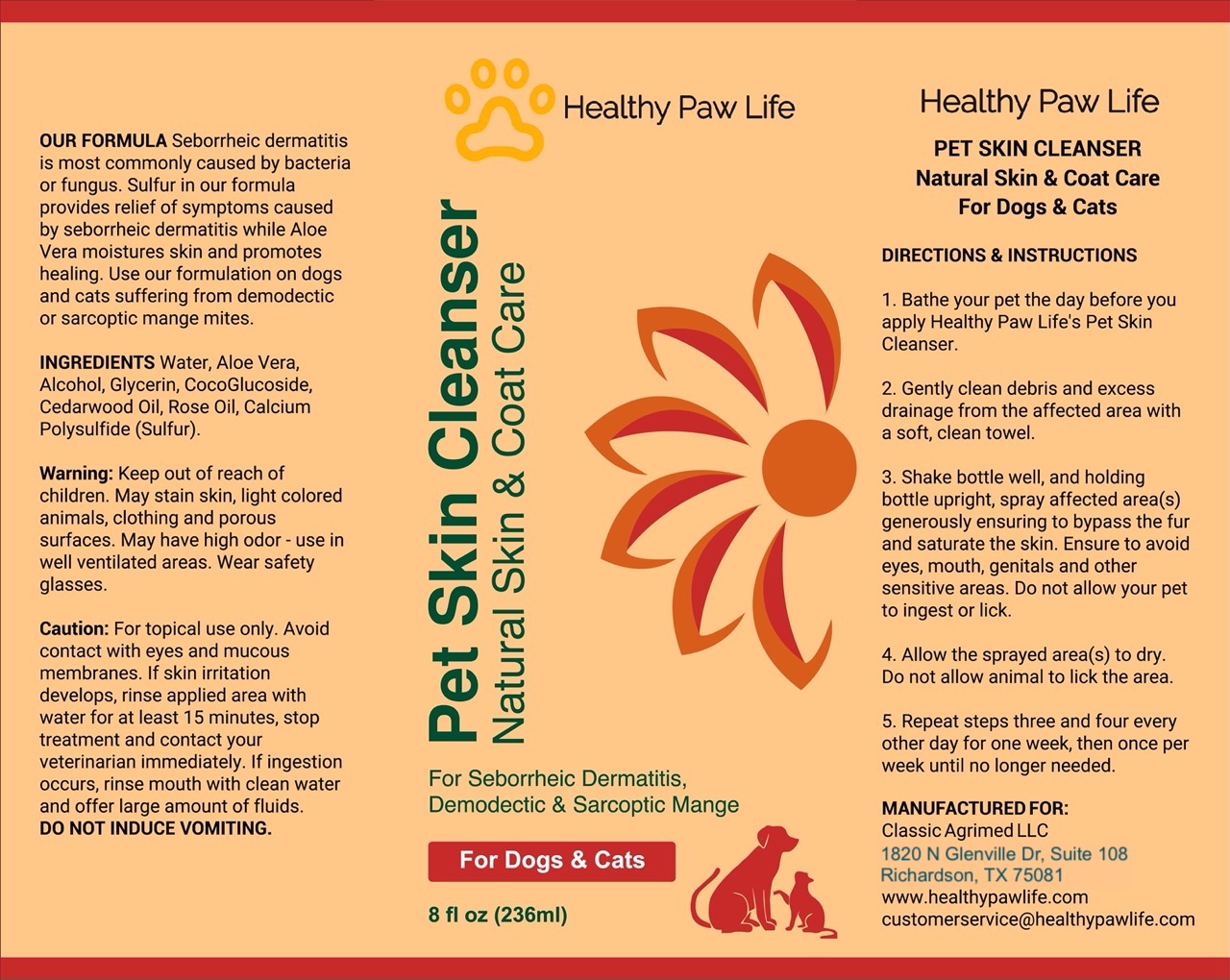 DRUG LABEL: HEALTHY PAW LIFE PET SKIN CLEANSER
NDC: 86130-900 | Form: SPRAY
Manufacturer: CLASSIC AGRIMED LLC
Category: animal | Type: OTC ANIMAL DRUG LABEL
Date: 20231118

ACTIVE INGREDIENTS: CALCIUM POLYSULFIDE 0.49 g/100 g

HEALTHY PAW LIFE PET SKIN CLEANSER

OUR FORMULA Seborrheic dermatitis is most commonly caused by bacteria or fungus. Sulfur in our formula provides relief of symptoms caused by seborrheic dermatitis while Aloe Vera moistures skin and promotes healing. Use our formulation on dogs and cats suffering from demodectic or sarcoptic mange mites.

INGREDIENTS Water, Aloe Vera, Alcohol, Glycerin, CocoGlucoside, Cedarwood Oil, Rose Oil, Calcium Polvsulfide (Sulfur).

Warning: Keep out of reach of children. May stain skin, light colored animals, clothing and porous surfaces. May have high odor - use in well ventilated areas. Wear safety glasses.

Caution: For topical use only. Avoid contact with eyes and mucous membranes. If skin irritation develops, rinse applied area with water for at least 15 minutes, stop treatment and contact your veterinarian immediately. If ingestion occurs, rinse mouth with clean water and offer large amount of fluids.
DO NOT INDUCE VOMITING.

DIRECTIONS & INSTRUCTIONS
1. Bathe your pet the day before you apply Healthy Paw Life's Pet Skin
Cleanser.
2. Gently clean debris and excess drainage from the affected area with a soft, clean towel.
3. Shake bottle well, and holding bottle upright, spray affected area(s) generously ensuring to bypass the fur and saturate the skin. Ensure to avoid eyes, mouth, genitals and other sensitive areas. Do not allow your pet to ingest or lick.
4. Allow the sprayed areas to dry.
Do not allow animal to lick the area.
5. Repeat steps three and four every other day for one week, then once per week until no longer needed.

MANUFACTURED FOR:
Classic Agrimed LLC